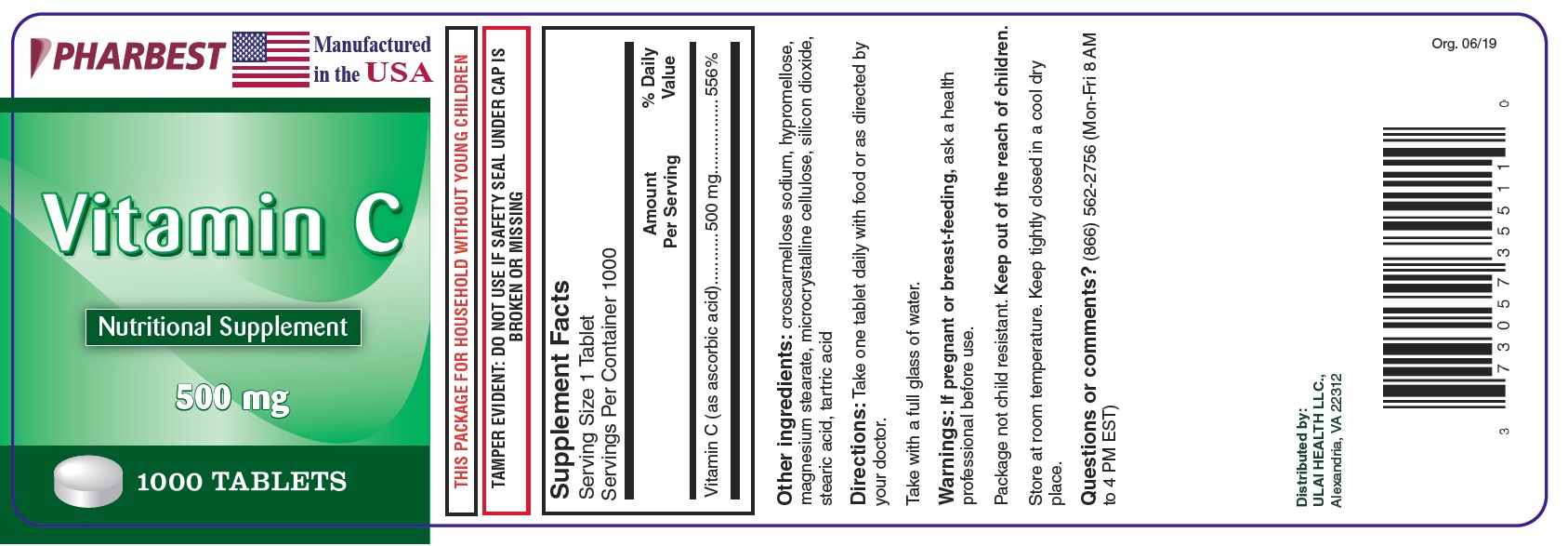 DRUG LABEL: Vitamin C
NDC: 73057-355 | Form: TABLET
Manufacturer: Ulai Health LLC
Category: other | Type: DIETARY SUPPLEMENT
Date: 20190717

ACTIVE INGREDIENTS: ASCORBIC ACID 500 mg/1 1
INACTIVE INGREDIENTS: CROSCARMELLOSE SODIUM; HYPROMELLOSE, UNSPECIFIED; MAGNESIUM STEARATE; CELLULOSE, MICROCRYSTALLINE; SILICON DIOXIDE; STEARIC ACID; TARTARIC ACID

Supplement Facts

Supplement Facts

Serving Size 1 Tablet

Servings Per Container 1000

 | Amount Per Serving | % Daily Value
Vitamin C (as ascorbic acid) | 500 mg | 556%

Other ingredients: croscarmellose sodium, hypromellose, magnesium stearate, microcrystalline cellulose, silicon dioxide, stearic acid, tartaric acid

DOSAGE AND ADMINISTRATION

Take one tablet daily with food or as directed by your doctor.

Take with a full glass of water.

WARNINGS

If pregnant or breast-feeding, ask a health professional before use.

Package not child resistant.

Keep out of the reach of children.

SAFE HANDLING WARNING

Store at room temperature. Keep tightly closed in a cool dry place.

Questions or Comments? (866) 562-2756 (Mon-Fri 8 AM to 4 PM EST)

PACKAGE LABEL

PHARBEST

Manufactured in the USA

Vitamin C

Nutritional Supplement

500 mg

1000 TABLETS